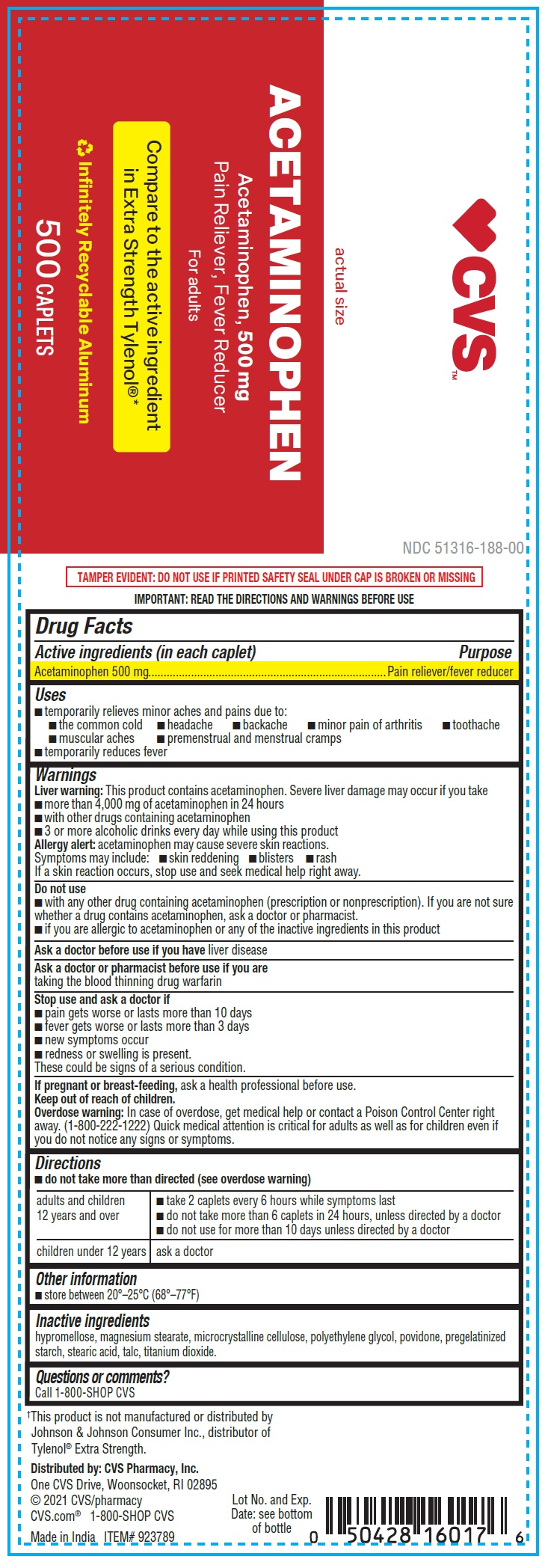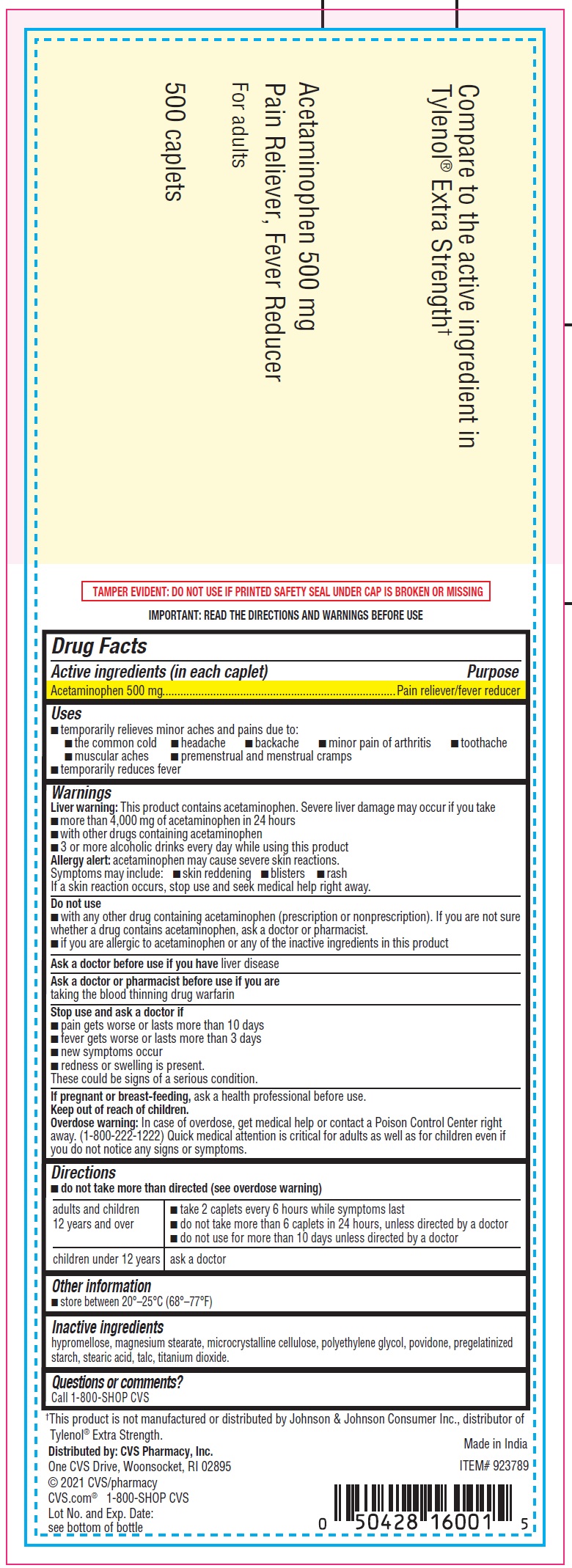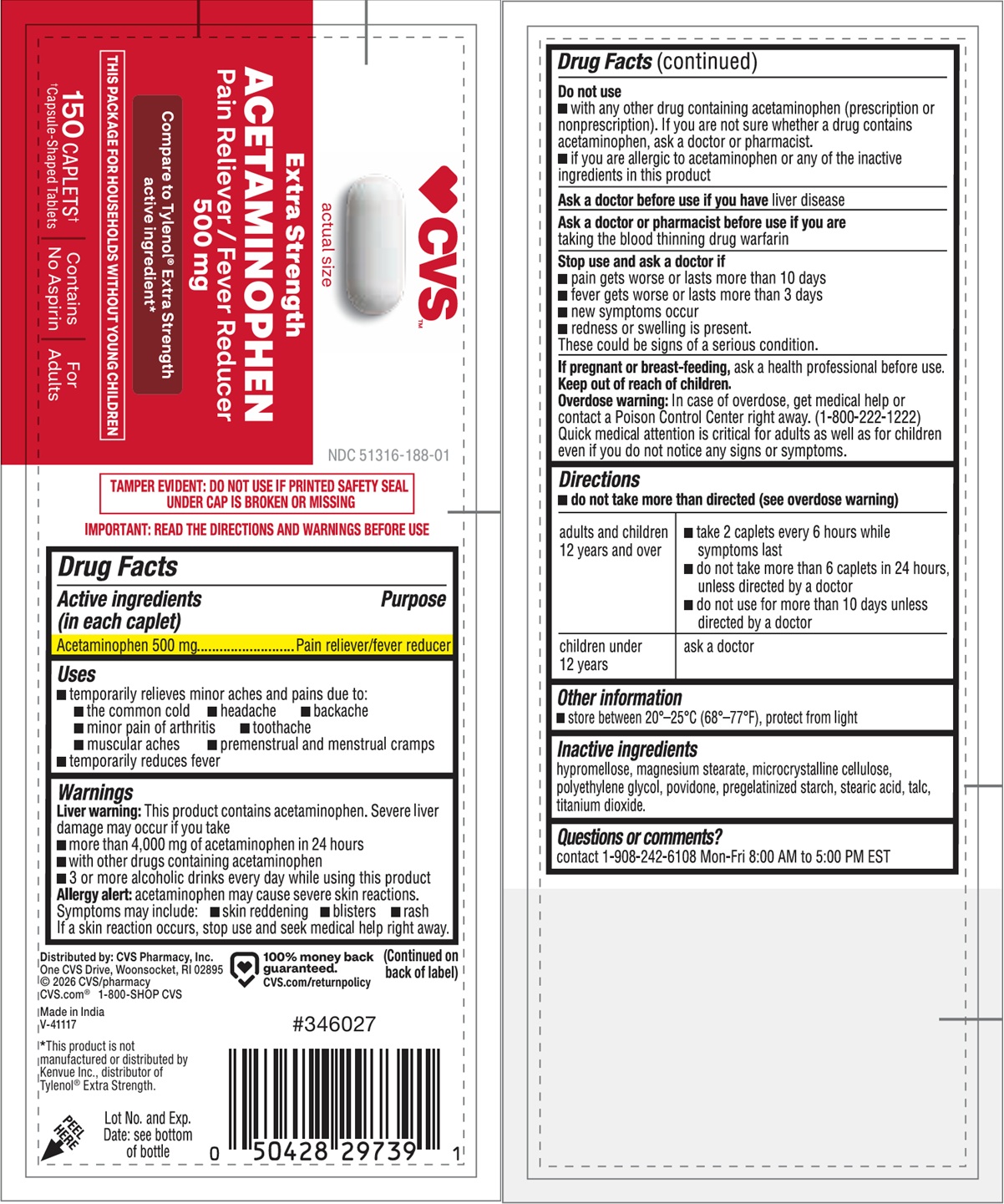 DRUG LABEL: CVS Acetaminophen
NDC: 51316-188 | Form: CAPSULE
Manufacturer: CVS Pharmacy
Category: otc | Type: HUMAN OTC DRUG LABEL
Date: 20260211

ACTIVE INGREDIENTS: ACETAMINOPHEN 500 mg/1 1
INACTIVE INGREDIENTS: HYPROMELLOSE, UNSPECIFIED; MAGNESIUM STEARATE; MICROCRYSTALLINE CELLULOSE; POLYETHYLENE GLYCOL, UNSPECIFIED; POVIDONE; STEARIC ACID; TALC; TITANIUM DIOXIDE

CVS Acetaminophen

Active ingredient (in each tablet)

Acetaminophen 500 mg

Purpose

Pain reliever/fever reducer

Uses

• temporarily relieves minor aches and pains due to: • the common cold • headache • backache • minor pain of arthritis • toothache • muscular aches • premenstrual and menstrual cramps

• temporarily reduces fever

Warnings

Liver warning:This product contains acetaminophen. Severe liver damage may occur if you take

- more than 4,000 mg of acetaminophen in 24 hours
- with other drugs containing acetaminophen
- 3 or more alcoholic drinks every day while using this product

Allergy alert:acetaminophen may cause severe skin reactions. Symptoms may include: •skin reddening •blisters •rash

If a skin reaction occurs, stop use and seek medical help right away.

Do not use

- with any other drug containing acetaminophen (prescription or nonprescription). If you are not sure whether a drug contains acetaminophen, ask a doctor or pharmacist.
- if you are allergic to acetaminophen or any of the inactive ingredients in this product

Ask a doctor before use if you have

liver disease

Ask a doctor or pharmacist before use if you are

taking the blood thinning drug warfarin

Stop use and ask a doctor if

- pain gets worse or lasts more than 10 days
- fever gets worse or lasts more than 3 days
- new symptoms occur
- redness or swelling is present. These could be signs of a serious condition.

If pregnant or breast-feeding,

ask a health professional before use.

Keep out of reach of children.

Overdose warning:In case of overdose, get medical help or contact a Poison Control Center right away. (1-800-222-1222) Quick medical attention is critical for adults as well as for children even if you do not notice any signs or symptoms.

Directions

- do not take more than directed (see overdose warning)

adults and children 12 years and over | - take 2 caplets every 6 hours while symptoms last - do not take more than 6 caplets in 24 hours, unless directed by a doctor - do not use for more than 10 days unless directed by a doctor
children under 12 years | ask a doctor

Other information

- store between 20°–25°C (68°–77°F), protect from light

Inactive ingredients

hypromellose, magnesium stearate, microcrystalline cellulose, polyethylene glycol, povidone, pregelatinized starch, stearic acid, talc, titanium dioxide.

Questions or comments?

Call 1-908-242-6108 Mon-Fri 8:00 AM to 5:00 PM EST